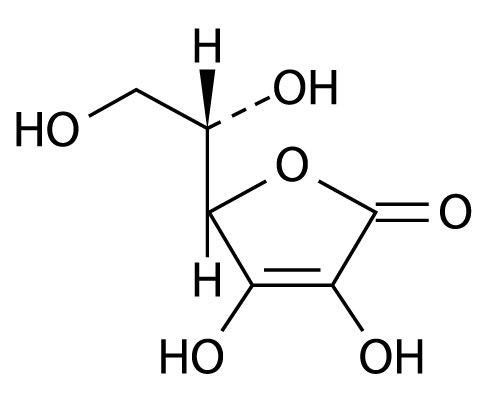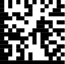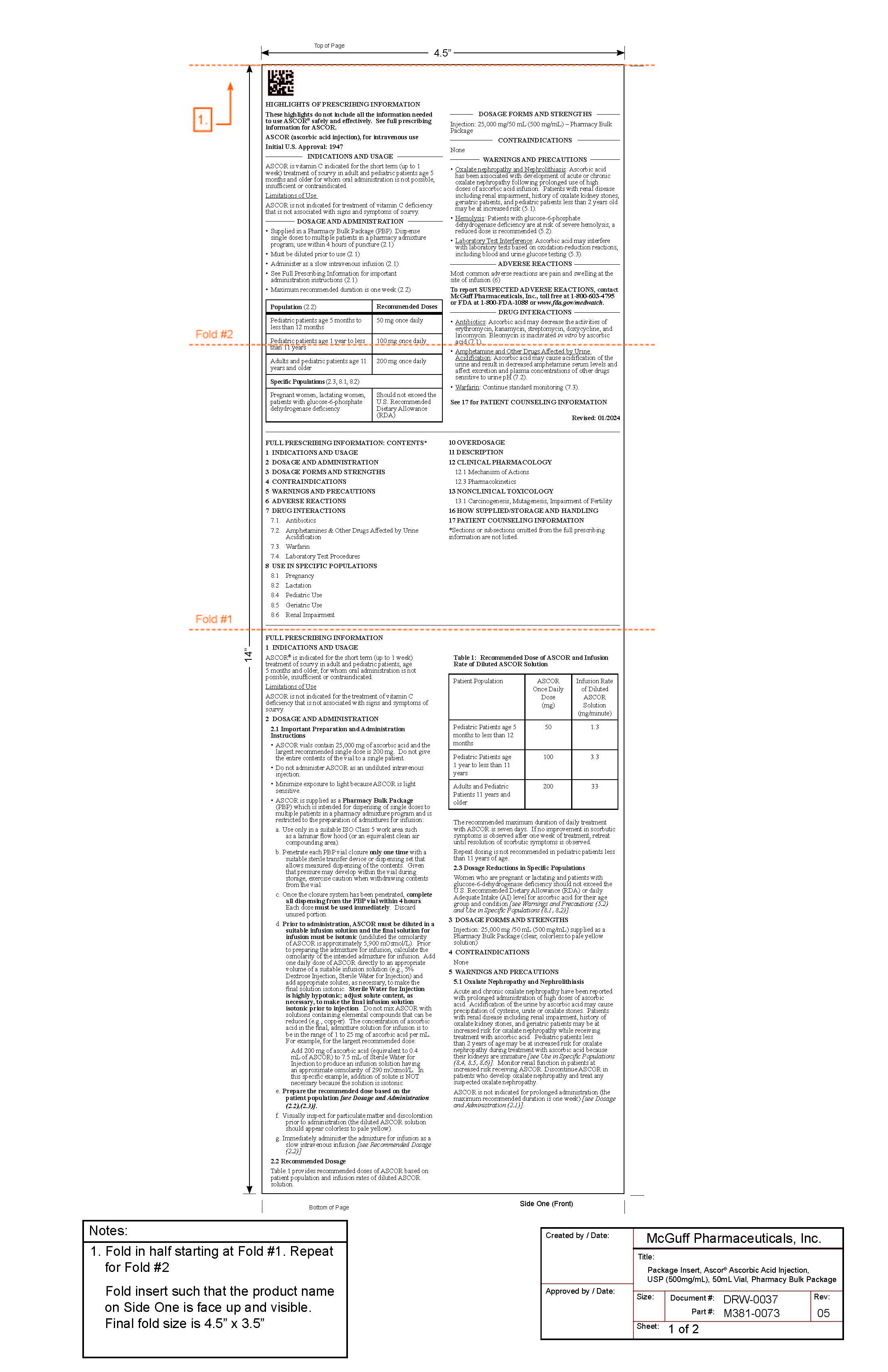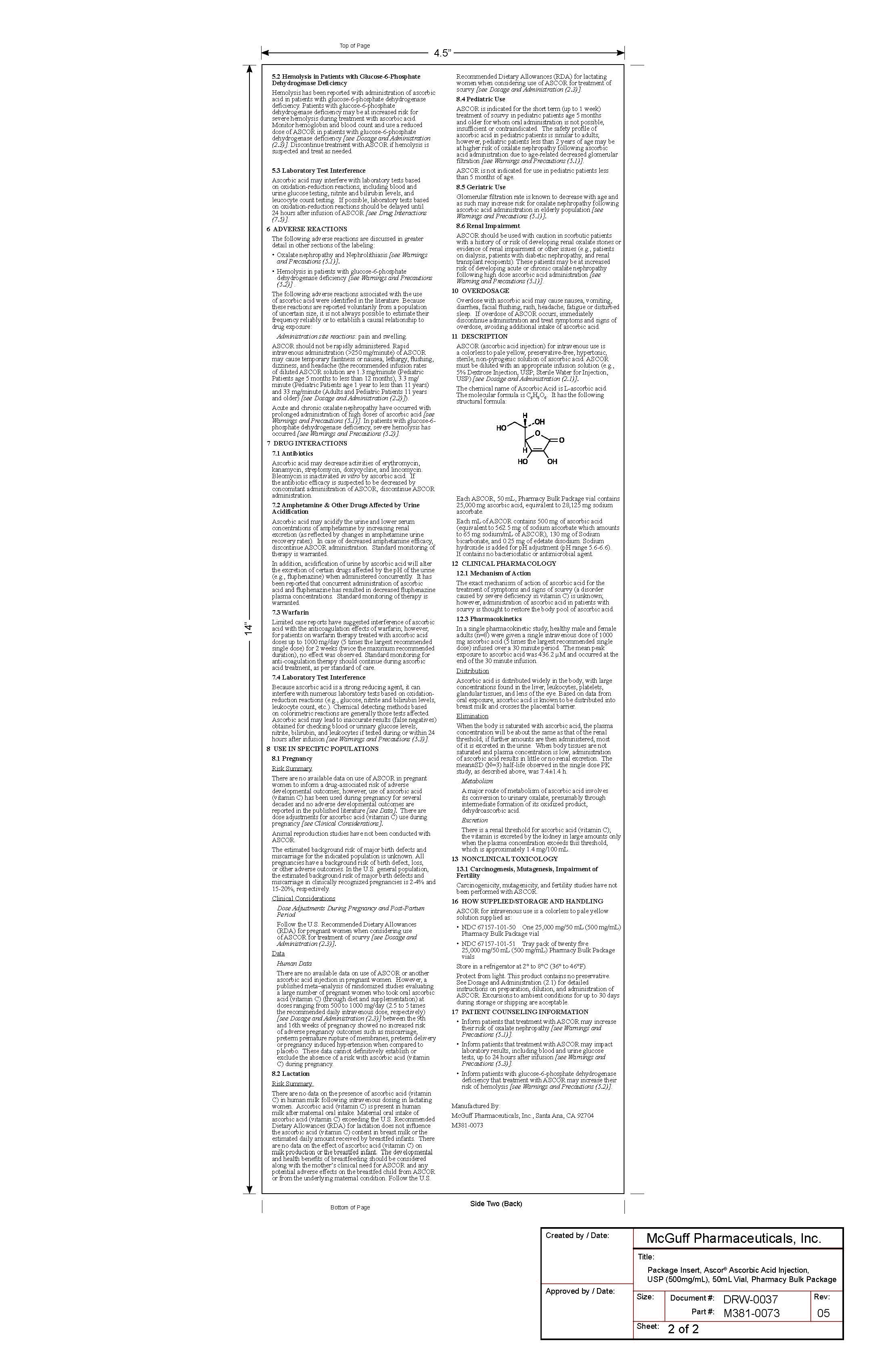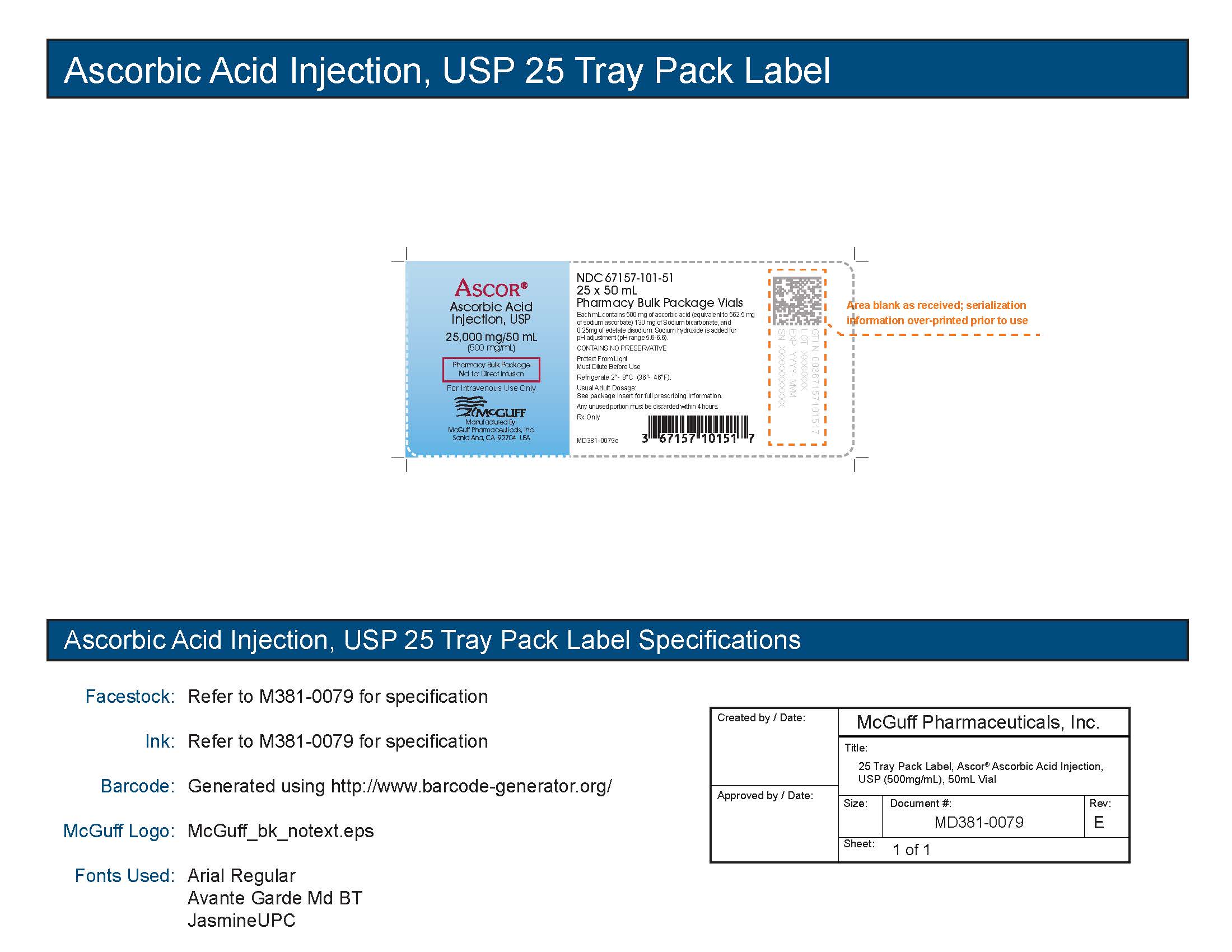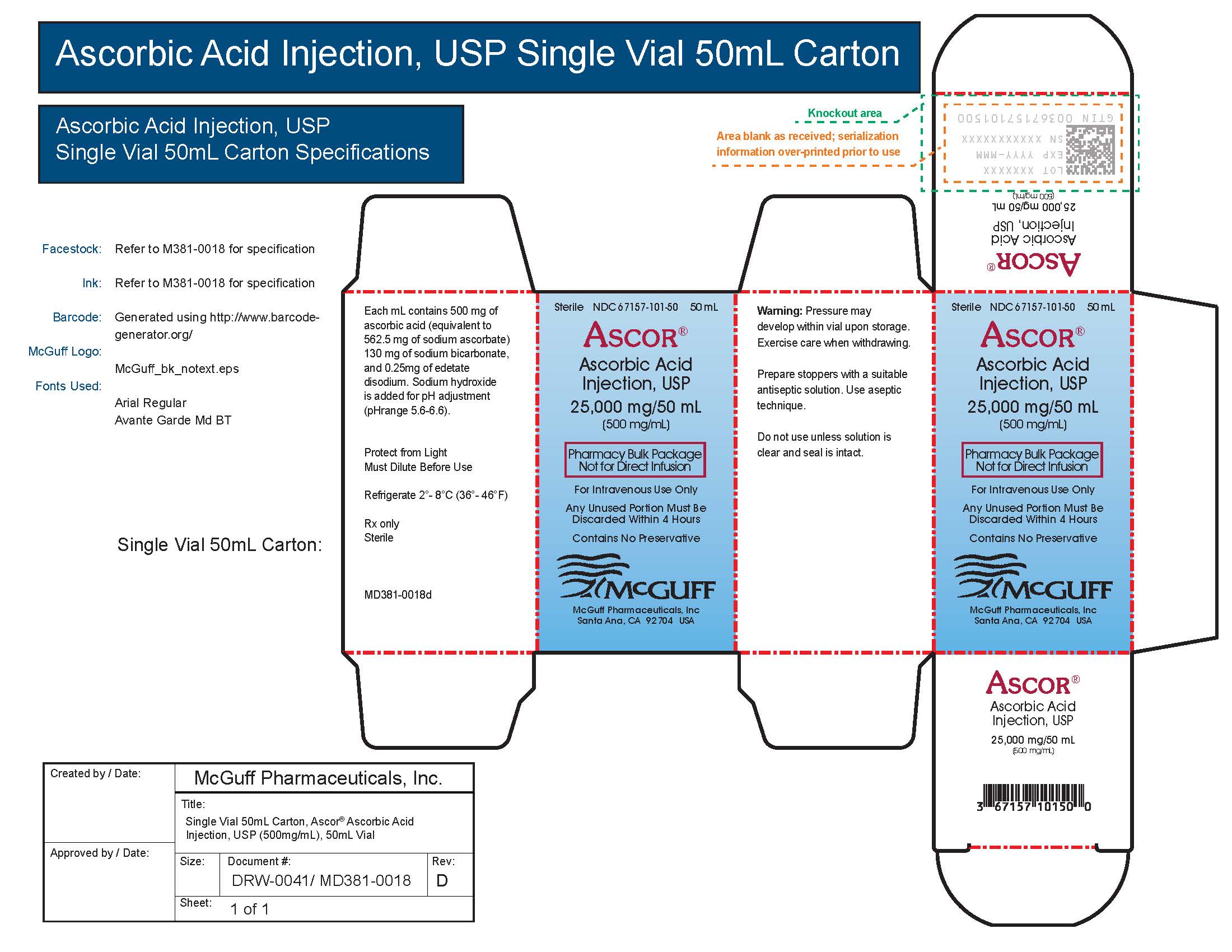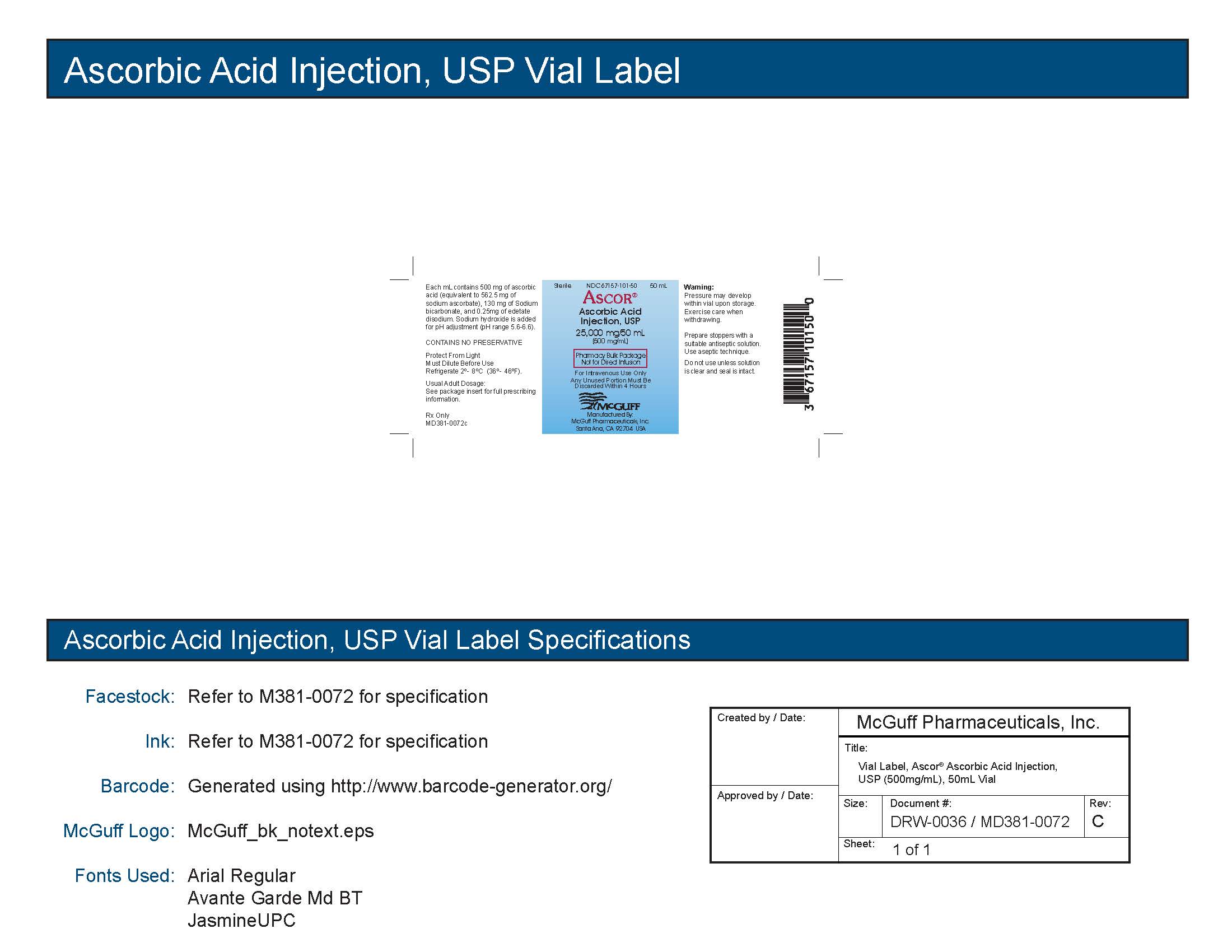 DRUG LABEL: Ascor
NDC: 67157-101 | Form: INJECTION
Manufacturer: McGuff Pharmaceuticals, Inc.
Category: prescription | Type: HUMAN PRESCRIPTION DRUG LABEL
Date: 20251119

ACTIVE INGREDIENTS: ASCORBIC ACID 500 mg/1 mL
INACTIVE INGREDIENTS: EDETATE DISODIUM 0.25 mg/1 mL; SODIUM HYDROXIDE; SODIUM BICARBONATE

HIGHLIGHTS OF PRESCRIBING INFORMATION

ASCOR HIGHLIGHTS OF PRESCRIBING INFORMATION
These highlights do not include all the information needed to use ASCOR® safely and effectively. See full prescribing information for ASCOR.
ASCOR (ascorbic acid injection), for intravenous use Initial U.S. Approval: 1947
Initial U.S. Approval: 1947

1. INDICATIONS AND USAGE

ASCOR is vitamin C indicated for the short term (up to 1 week) treatment of scurvy in adult and pediatric patients age 5 months and older for whom oral administration is not possible, insufficient or contraindicated.

Limitations of Use

ASCOR is not indicated for treatment of vitamin C deficiency that is not associated with signs and symptoms of scurvy.

2. DOSAGE AND ADMINISTRATION

- Supplied in Pharmacy Bulk Package (PBP). Dispense single doses to multiple patients in a pharmacy admixture program; use within 4 hours of puncture. (2.1)
- Must be diluted prior to use (2.1)
- Administer as a slow intravenous infusion (2.1)
- See Full Prescribing Information for important administration instructions (2.1)
- Maximum recommended duration is one week (2.2)

Population (2.2) | Recommended Doses
Pediatric patients age 5 months to less than 12 months | 50 mg once daily
Pediatric patients age 1 year to less than 11 years | 100 mg once daily
Adults and pediatric patients age 11 years and older | 200 mg once daily
Specific Populations (2.3, 8.1, 8.2)
Pregnant women, lactating women, patients with glucose-6-phosphate dehydrogenase deficiency | Should not exceed the U.S. Recommended Dietary Allowance (RDA)

2.1 Important Preparation and Administration Instructions

ASCOR vials contain 25, 000 mg of ascorbic acid and the largest recommended single dose is 200 mg. Do not give the entire contents of the vial to a single patient.
Do not administer ASCOR as an undiluted intravenous sensitive.
Minimize exposure to light because ASCOR is light sensitive.
ASCOR is supplied as a Pharmacy Bulk Package (PBP) which is intended for dispensing of single doses to multiple patients in a pharmacy admixture program and is restricted to the preparation of admixtures for infusion:

a. Use only in a suitable ISO Class 5 work area such as a laminar flow hood (or an equivalent clean air compounding area)

b. Penetrate each PBP vial closure only one time with a suitable sterile transfer device or dispensing set that allows measured dispensing of the contents. Given that pressure may develop within the vial during storage, excercise caution when withdrawing contents from the vial.

c. Once the closure system has been penetrated, complete all dispensing from the PBP vial within 4 hours. Each dose must be used immediately. Discard unused portion.

d. Prior to administration, ASCOR must be diluted in a suitable infusion solution and the final solution for infusion must be isotonic (undiluted the osmolarity of ASCOR is approximately 5,900 mOsmol/L). Prior to preparing the admixture for infusion, calculate the osmolarity of the intended admixture for infusion. Add one daily dose of ASCOR directly to an appropriate volume of a suitable infusion solution (e.g., 5% Dextrose Injection, Sterile Water for Injection) and add appropriate solutes, as necessary, to make final solution isotonic. Sterile Water for Injection is highly hypotonic; adjust solute content, as necessary, to make thet final infusion solution isotonic prior to injection. Do not mix ASCOR with solutions containing elemental compounds that can be reduced (e.g., copper). The concentration of ascorbic acid in the final, admixture solution for infusion is to be the range of 1 to 25 mg of ascorbic acid per mL. For example, for the largest recommended dose:

Add 200 mg of ascorbic acid (equivalent to 0.4 mL of ASCOR) to 7.5 mL of Sterile Water for Injection to produce an infusion solution having an approximate osmolarity of 290 mOsmol/L. In this specific example, addition of solute is NOT necessary because the solution is isotonic.

e. Prepare the recommended dose based on the patient population [ see Dosage and Administration (2.2), (2.3)].

f. Visually inspect for particulate matter and discoloration prior to administration (the diluted ASCOR solution should appear colorless to pale yellow).

g. Immediately administer the admixture for infusion as a slow intravenous infusion [ see Recommended Dosage, (2.2)]

3. DOSAGE FORMS AND STRENGTHS

Injection: 25,000 mg /50 mL (500 mg/mL) supplied as a Pharmacy Bulk Package (clear, colorless to pale yellow solution)

4. CONTRAINDICATIONS

None.

5. WARNINGS AND PRECAUTIONS

- Oxalate nephropathy and Nephrolithiasis: Ascorbic acid has been associated with development of acute or chronic oxalate nephropathy following prolonged use of high doses of ascorbic acid infusion. Patients with renal disease including renal impairment, history of oxalate kidney stones, geriatric patients, and pediatric patients less than 2 years old may be at increased risk (5.1).
- Hemolysis: Patients with glucose-6-phosphate dehydrogenase deficiency are at risk of severe hemolysis; a reduced is recommended (5.2).
- Laboratory Test Interference: Ascorbic acid may interfere with laboratory tests based on oxidation-reduction reactions, including blood and urine glucose testing (5.3).

6. ADVERSE REACTIONS

Most common adverse reactions are pain and swelling at the site of infusion (6)

To report SUSPECTED ADVERSE REACTIONS, contact McGuff Pharmaceuticals, Inc., toll free at 1-800-603-4795 or FDA at 1-800-FDA-1088 or www.fda.gov/medwatch.

7. DRUG INTERACTIONS

- Antibiotics: Ascorbic acid may decrease the activities of erythromycin, kanamycin, streptomycin, doxycycline, and lincomycin. Bleomycin is inactivated in vitro by ascorbic acid (7.1).
- Amphetamine and Other Drugs Affected by Urine Acidification: Ascorbic acid may cause acidification of the urine and result in decreased amphetamine serum levels affect excretion and plasma concentrations of other drugs sensitive to urine pH (7.2).
- Warfarin: Continue standard monitoring (7.3)

See 17 for PATIENT COUNSELING INFORMATION

7.1 Antibiotics

Ascorbic acid may decrease activities of erythromycin, kanamycin, streptomycin, doxycycline, and lincomycin. Bleomycin is inactivated in vitro by ascorbic acid. If the antibiotic efficacy is suspected to be decreased by concomitant administration of ASCOR, discontinue ASCOR administration.

7.2 Amphetamine & Other Drugs Affected by Urine Acidification

Ascorbic acid may acidify the urine and lower serum concentrations of amphetamine by increasing renal excretion (as reflected by changes in amphetamine urine recovery rates). In case of decreased amphetamine efficacy discontinue ASCOR administration. Standard monitoring of therapy is warranted.

In addition, acidification of urine by ascorbic acid will alter the excretion of certain drugs affected by the pH of the urine (e.g., fluphenazine) when administered concurrently. It has been reported that concurrent administration of ascorbic acid and fluphenazine has resulted in decreased fluphenazine plasma concentrations. Standard monitoring of therapy is warranted.

7.3 Warfarin

Limited case reports have suggested interference of ascorbic acid with the anticoagulation effects of warfarin, however, patients on warfarin therapy treated with ascorbic acid doses up to 1000 mg/day (5 times the largest recommended single dose) for 2 weeks (twice the maximum recommended duration), no effect was observed. Standard monitoring for anti-coagulation therapy should continue during ascorbic acid treatment, as per standard of care.

7.4 Laboratory Test Interference

Because ascorbic acid is a strong reducing agent, it can interfere with numerous laboratory tests based on oxidation-reduction reactions (e.g., glucose, nitrite and bilirubin levels, leukocyte count, etc.). Chemical detecting methods based on colorimetric reactions are generally those tests affected. Ascorbic acid may lead to inaccurate results (false negatives) obtained for checking blood or urinary glucose levels, nitrite, bilirubin, and leukocytes if tested during or within 24 hours after infusion [see Warnings and Precautions (5.3)] .

8. USE IN SPECIFIC POPULATIONS

USE IN SPECIFIC POPULATIONS

8.1 Pregnancy

8.2 Lactation

8.4 Pediatric Use

8.5 Geriatric Use

8.6 Renal Impairment

8.1 Pregnancy

Risk Summary

There are no available data on use of ASCOR in pregnant women to inform a drug-associated risk of adverse developmental outcomes; however, use of ascorbic acid (vitamin C) has been used during pregnancy for several decades and no adverse developmental outcomes are reported in the published literature [see Data]. There are dose adjustments for ascorbic acid (vitamin C) use during pregnancy [ see Clinical Considerations].

Animal reproduction studies have not been conducted with ASCOR.

The estimated background risk of major birth defects and miscarriage for the indicated population is unknown. All pregnancies have a background risk of birth defect, loss, or other adverse outcomes. In the U.S. general population, the estimated background risk of major birth defects and miscarriage in clinically recognized pregnancies is 2-4% and 15-20%, respectively.

Clinical Considerations

Dose Adjustments During Pregnancy and Post-Partum Period

Follow the U.S. Recommended Dietary Allowances (RDA) for pregnant women when considering use of ASCOR for treatment of scurvy [ see Dosage and Administration (2.3)].

Data

Human Data

There are no available data on use of ASCOR or another ascorbic acid injection in pregnant women. However, a published meta–analysis of randomized studies evaluating a large number of pregnant women who took oral ascorbic acid (vitamin C) (through diet and supplementation) at doses ranging from 500 to1000 mg/day (2.5 to 5 times the recommended daily intravenous dose, respectively) [see Dosage and Administration (2.3)] between the 9th and 16th weeks of pregnancy showed no increased risk of adverse pregnancy outcomes such as miscarriage, preterm premature rupture of membranes, preterm delivery or pregnancy induced hypertension when compared to placebo. These data cannot definitely establish or exclude the absence of a risk with ascorbic acid (vitamin C) during pregnancy.

8.2 Lactation

Risk Summary

There are no data on the presence of ascorbic acid (vitamin C) in human milk following intravenous dosing in lactating women. Ascorbic acid (vitamin C) is present in human milk after maternal oral intake. Maternal oral intake of ascorbic acid (vitamin C) exceeding the U.S. Recommended Dietary Allowances (RDA) for lactation does not influence the ascorbic acid (vitamin C) content in breast milk or the estimated daily amount received by breastfed infants. There are no data on the effect of ascorbic acid (vitamin C) on milk production or the breastfed infant. The developmental and health benefits of breastfeeding should be considered along with the mother’s clinical need for ASCOR and any potential adverse effects on the breastfed child from ASCOR or from the underlying maternal condition. Follow the U.S. Recommended Dietary Allowances (RDA) for lactating women when considering use of ASCOR for treatment of scurvy [ see Dosage and Administration (2.3)].

8.4 Pediatric Use

ASCOR is indicated for the short term (up to 1 week) treatment of scurvy in pediatric patients age 5 months and older for whom oral administration is not possible, insufficient or contraindicated. The safety profile of ascorbic acid in pediatric patients is similar to adults; however, pediatric patients less than 2 years of age may be at higher risk of oxalate nephropathy following ascorbic acid administration due to age-related decreased glomerular filtration [ see Warnings and Precautions (5.1)].

Ascor is not indicated for use in pediatric patients less than 5 months of age.

8.5 Geriatric Use

Glomerular filtration rate is known to decrease with age and as such may increase risk for oxalate nephropathy following ascorbic acid administration in elderly population [ see Warnings and Precautions (5.1) ].

8.6 Renal Impairment

ASCOR should be used with caution in scorbutic patients with a history of or risk of developing renal oxalate stones or evidence of renal impairment or other issues (e.g., patients on dialysis, patients with diabetic nephropathy, and renal transplant recipients). These patients may be at increased risk of developing acute or chronic oxalate nephropathy following high dose ascorbic acid administration [see Warning and Precaution (5.1].

FULL PRESCRIBING INFORMATION

HIGHLIGHTS OF PRESCRIBING INFORMATION

These highlights do not include all the information needed to use ASCOR® safely and effectively. See full prescribing information for ASCOR.

ASCOR (ascorbic acid injection), for intravenous use Initial U.S. Approval: 1947

1. INDICATIONS AND USAGE

ASCOR is vitamin C indicated for the short term (up to 1 week) treatment of scurvy in adult and pediatric patients age 5 months and older for whom oral administration is not possible, insufficient or contraindicated.

Limitations of Use

ASCOR is not indicated for treatment of vitamin C deficiency that is not associated with signs and symptoms of scurvy.

2. DOSAGE AND ADMINISTRATION

- Supplied in Pharmacy Bulk Package (PBP). Dispense single doses to multiple patients in a pharmacy admixture program; use within 4 hours of puncture. (2.1)
- Must be diluted prior to use (2.1)
- Administer as a slow intravenous infusion (2.1)
- See Full Prescribing Information for important administration instructions (2.1)
- Maximum recommended duration is one week (2.2)

Population (2.2) | Recommended Doses
Pediatric patients age 5 months to less than 12 months | 50 mg once daily
Pediatric patients age 1 year to less than 11 years | 100 mg once daily
Adults and pediatric patients age 11 years and older | 200 mg once daily
Specific Populations (2.3, 8.1, 8.2)
Pregnant women, lactating women, patients with glucose-6-phosphate dehydrogenase deficiency | Should not exceed the U.S. Recommended Dietary Allowance (RDA)

2.1 Important Preparation and Administration Instructions

- ASCOR vials contain 25, 000 mg of ascorbic acid and the largest recommended single dose is 200 mg. Do not give the entire contents of the vial to a single patient.
- Do not administer ASCOR as an undiluted intravenous sensitive.
- Minimize exposure to light because ASCOR is light sensitive.
- ASCOR is supplied as a Pharmacy Bulk Package (PBP) which is intended for dispensing of single doses to multiple patients in a pharmacy admixture program and is restricted to the preparation of admixtures for infusion:

a. Use only in a suitable ISO Class 5 work area such as a laminar flow hood (or an equivalent clean air compounding area)

b. Penetrate each PBP vial closure only one time with a suitable sterile transfer device or dispensing set that allows measured dispensing of the contents. Given that pressure may develop within the vial during storage, excercise caution when withdrawing contents from the vial.

c. Once the closure system has been penetrated, complete all dispensing from the PBP vial within 4 hours. Each dose must be used immediately. Discard unused portion.

d. Prior to administration, ASCOR must be diluted in a suitable infusion solution and the final solution for infusion must be isotonic (undiluted the osmolarity of ASCOR is approximately 5,900 mOsmol/L). Prior to preparing the admixture for infusion, calculate the osmolarity of the intended admixture for infusion. Add one daily dose of ASCOR directly to an appropriate volume of a suitable infusion solution (e.g., 5% Dextrose Injection, Sterile Water for Injection) and add appropriate solutes, as necessary, to make final solution isotonic. Sterile Water for Injection is highly hypotonic; adjust solute content, as necessary, to make thet final infusion solution isotonic prior to injection. Do not mix ASCOR with solutions containing elemental compounds that can be reduced (e.g., copper). The concentration of ascorbic acid in the final, admixture solution for infusion is to be the range of 1 to 25 mg of ascorbic acid per mL. For example, for the largest recommended dose:

Add 200 mg of ascorbic acid (equivalent to 0.4 mL of ASCOR) to 7.5 mL of Sterile Water for Injection to produce an infusion solution having an approximate osmolarity of 290 mOsmol/L. In this specific example, addition of solute is NOT necessary because the solution is isotonic.

e. Prepare the recommended dose based on the patient population [ see Dosage and Administration (2.2), (2.3)].

f. Visually inspect for particulate matter and discoloration prior to administration (the diluted ASCOR solution should appear colorless to pale yellow).

g. Immediately administer the admixture for infusion as a slow intravenous infusion [ see Recommended Dosage, (2.2)]

2.2 Recommended Dosage

Table 1 provides recommended doses of ASCOR based on patient population and infusion rates of diluted ASCOR solution.

Table 1: Recommended Dose of ASCOR and Infusion Rate of Diluted ASCOR Solution
Patient Population | ASCOR Once Daily Dose (mg) | Infusion Rate of Diluted ASCOR Solution (mg/minute)
Pediatric Patients age 5 months to less than 12 months | 50 | 1.3
Pediatric Patients age 1 year to less than 11 years | 100 | 3.3
Adults and Pediatric Patients 11 years and older | 200 | 33

The recommended maximum duration of daily treatment with ASCOR is seven days. If no improvement in scorbutic symptoms is observed after one week of treatment, retreat until resolution of scorbutic symptoms is observed.

Repeat dosing is not recommended in pediatric patients less than 11 years of age.

2.3 Dosage Reductions in Specific Populations

Women who are pregnant or lactating and patients with glucose-6-dehydrogenase deficiency should not exceed the U.S. Recommended Dietary Allowance (RDA) or daily Adequate Intake (AI) level for ascorbic acid for their age group and condition [ see Warnings and Precautions (5.2) and Use in Specific Populations (8.1, 8.2)].

3. DOSAGE FORMS AND STRENGTHS

Injection: 25,000 mg/50 mL (500 mg/mL) - Pharmacy Bulk Package

4. CONTRAINDICATIONS

None.

5. WARNINGS AND PRECAUTIONS

5.1 Oxalate Nephropathy and Nephrolithiasis

Acute and chronic oxalate nephropathy have been reported with prolonged administration of high doses of ascorbic acid. Acidification of the urine by ascorbic acid may cause precipitation of cysteine, urate or oxalate stones. Patients with renal disease including renal impairment, history of oxalate kidney stones, and geriatric patients may be at increased risk for oxalate nephropathy while receiving treatment with ascorbic acid. Pediatric patients less than 2 years of age may be at increased risk for oxalate nephropathy during treatment with ascorbic acid because their kidneys are immature [see Use in Specific Populations (8.4, 8.5, 8.6)]. Monitor renal function in patients at increased risk receiving ASCOR. Discontinue ASCOR in patients who develop oxalate nephropathy and treat any suspected oxalate nephropathy.

ASCOR is not indicated for prolonged administration (the maximum recommended duration is one week) [see Dosage and Administration (2.1)] .

5.2 Hemolysis in Patients with Glucose-6-Phosphate Dehydrogenase Deficiency

Hemolysis has been reported with administration of ascorbic acid in patients with glucose-6-phosphate dehydrogenase deficiency. Patients with glucose-6-phosphate dehydrogenase deficiency may be at increased risk for severe hemolysis during treatment with ascorbic acid. Monitor hemoglobin and blood count and use a reduced dose of ASCOR in patients with glucose-6-phosphate dehydrogenase deficiency [see Dosage and Administration (2.3)]. Discontinue treatment with ASCOR if hemolysis is suspected and treat as needed.

5.3 Laboratory Test Interference

Ascorbic acid may interfere with laboratory tests based on oxidation-reduction reactions, including blood and urine glucose testing, nitrite and bilirubin levels, and leucocyte count testing. If possible, laboratory tests based on oxidation-reduction reactions should be delayed until 24 hours after infusion of ASCOR [see Drug Interactions (7.4)].

6. ADVERSE REACTIONS

The following adverse reactions are discussed in greater detail in other sections of the labeling:

Oxalate nephropathy and Nephrolithiasis [see Warnings and Precautions (5.1)]
Hemolysis in patients with glucose-6-phosphate dehydrogenase deficiency [see Warnings and Precautions (5.2)]

The following adverse reactions associated with the use of ascorbic acid were identified in the literature. Because these reactions are reported voluntarily from a population of uncertain size, it is not always possible to estimate their frequency reliably or to establish a causal relationship to drug exposure:

Administration site reactions: pain and swelling.

ASCOR should not be rapidly administered. Rapid intravenous administration (>250 mg/minute) of ASCOR may cause temporary faintness or nausea, lethargy, flushing, dizziness, and headache (the recommended infusion rates of diluted ASCOR solution are 1.3 mg/minute (Pediatric Patients age 5 months to less than 12 months), 3.3 mg/minute (Pediatric Patients age 1 year to less than 11 years) and 33 mg/minute (Adults and Pediatric Patients 11 years and older) [see Dosage and Administration (2.2)]).

Acute and chronic oxalate nephropathy have occurred with prolonged administration of high doses of ascorbic acid [see Warnings and Precautions (5.1)]. In patients with glucose-6-phosphate dehydrogenase deficiency severe hemolysis has occurred [see Warnings and Precautions (5.2)].

7. DRUG INTERACTIONS

Antibiotics: Ascorbic acid may decrease the activities of erythromycin, kanamycin, streptomycin, doxycycline, and lincomycin. Bleomycin is inactivated in vitro by ascorbic acid (7.1).
Amphetamine and Other Drugs Affected by Urine Acidification: Ascorbic acid may cause acidification of the urine and result in decreased amphetamine serum levels affect excretion and plasma concentrations of other drugs sensitive to urine pH (7.2).
Warfarin: Continue standard monitoring (7.3)

See 17 for PATIENT COUNSELING INFORMATION

7.1 Antibiotics

Ascorbic acid may decrease activities of erythromycin, kanamycin, streptomycin, doxycycline, and lincomycin. Bleomycin is inactivated in vitro by ascorbic acid. If the antibiotic efficacy is suspected to be decreased by concomitant administration of ASCOR, discontinue ASCOR administration.

7.2 Amphetamine & Other Drugs Affected by Urine Acidification

Ascorbic acid may acidify the urine and lower serum concentrations of amphetamine by increasing renal excretion (as reflected by changes in amphetamine urine recovery rates). In case of decreased amphetamine efficacy discontinue ASCOR administration. Standard monitoring of therapy is warranted.

In addition, acidification of urine by ascorbic acid will alter the excretion of certain drugs affected by the pH of the urine (e.g., fluphenazine) when administered concurrently. It has been reported that concurrent administration of ascorbic acid and fluphenazine has resulted in decreased fluphenazine plasma concentrations. Standard monitoring of therapy is warranted.

7.3 Warfarin

Limited case reports have suggested interference of ascorbic acid with the anticoagulation effects of warfarin, however, patients on warfarin therapy treated with ascorbic acid doses up to 1000 mg/day (5 times the largest recommended single dose) for 2 weeks (twice the maximum recommended duration), no effect was observed. Standard monitoring for anti-coagulation therapy should continue during ascorbic acid treatment, as per standard of care.

7.4 Laboratory Test Interference

Because ascorbic acid is a strong reducing agent, it can interfere with numerous laboratory tests based on oxidation-reduction reactions (e.g., glucose, nitrite and bilirubin levels, leukocyte count, etc.). Chemical detecting methods based on colorimetric reactions are generally those tests affected. Ascorbic acid may lead to inaccurate results (false negatives) obtained for checking blood or urinary glucose levels, nitrite, bilirubin, and leukocytes if tested during or within 24 hours after infusion [see Warnings and Precautions (5.3)] .

8. USE IN SPECIFIC POPULATIONS

USE IN SPECIFIC POPULATIONS

8.1 Pregnancy

8.2 Lactation

8.4 Pediatric Use

8.5 Geriatric Use

8.6 Renal Impairment

8.1 Pregnancy

Risk Summary

There are no available data on use of ASCOR in pregnant women to inform a drug-associated risk of adverse developmental outcomes; however, use of ascorbic acid (vitamin C) has been used during pregnancy for several decades and no adverse developmental outcomes are reported in the published literature [see Data]. There are dose adjustments for ascorbic acid (vitamin C) use during pregnancy [ see Clinical Considerations].

Animal reproduction studies have not been conducted with ASCOR.

The estimated background risk of major birth defects and miscarriage for the indicated population is unknown. All pregnancies have a background risk of birth defect, loss, or other adverse outcomes. In the U.S. general population, the estimated background risk of major birth defects and miscarriage in clinically recognized pregnancies is 2-4% and 15-20%, respectively.

Clinical Considerations

Dose Adjustments During Pregnancy and Post-Partum Period

Follow the U.S. Recommended Dietary Allowances (RDA) for pregnant women when considering use of ASCOR for treatment of scurvy [ see Dosage and Administration (2.3)].

Data

Human Data

There are no available data on use of ASCOR or another ascorbic acid injection in pregnant women. However, a published meta–analysis of randomized studies evaluating a large number of pregnant women who took oral ascorbic acid (vitamin C) (through diet and supplementation) at doses ranging from 500 to1000 mg/day (2.5 to 5 times the recommended daily intravenous dose, respectively) [ see Dosage and Administration (2.3)] between the 9th and 16th weeks of pregnancy showed no increased risk of adverse pregnancy outcomes such as miscarriage, preterm premature rupture of membranes, preterm delivery or pregnancy induced hypertension when compared to placebo. These data cannot definitely establish or exclude the absence of a risk with ascorbic acid (vitamin C) during pregnancy.

8.2 Lactation

Risk Summary

There are no data on the presence of ascorbic acid (vitamin C) in human milk following intravenous dosing in lactating women. Ascorbic acid (vitamin C) is present in human milk after maternal oral intake. Maternal oral intake of ascorbic acid (vitamin C) exceeding the U.S. Recommended Dietary Allowances (RDA) for lactation does not influence the ascorbic acid (vitamin C) content in breast milk or the estimated daily amount received by breastfed infants. There are no data on the effect of ascorbic acid (vitamin C) on milk production or the breastfed infant. The developmental and health benefits of breastfeeding should be considered along with the mother’s clinical need for ASCOR and any potential adverse effects on the breastfed child from ASCOR or from the underlying maternal condition. Follow the U.S. Recommended Dietary Allowances (RDA) for lactating women when considering use of ASCOR for treatment of scurvy [see Dosage and Administration (2.3)].

8.4 Pediatric Use

ASCOR is indicated for the short term (up to 1 week) treatment of scurvy in pediatric patients age 5 months and older for whom oral administration is not possible, insufficient or contraindicated. The safety profile of ascorbic acid in pediatric patients is similar to adults; however, pediatric patients less than 2 years of age may be at higher risk of oxalate nephropathy following ascorbic acid administration due to age-related decreased glomerular filtration [ see Warnings and Precautions (5.1)].

Ascor is not indicated for use in pediatric patients less than 5 months of age.

8.5 Geriatric Use

Glomerular filtration rate is known to decrease with age and as such may increase risk for oxalate nephropathy following ascorbic acid administration in elderly population [ see Warnings and Precautions (5.1) ].

8.6 Renal Impairment

ASCOR should be used with caution in scorbutic patients with a history of or risk of developing renal oxalate stones or evidence of renal impairment or other issues (e.g., patients on dialysis, patients with diabetic nephropathy, and renal transplant recipients). These patients may be at increased risk of developing acute or chronic oxalate nephropathy following high dose ascorbic acid administration [ see Warning and Precaution (5.1].

10. OVERDOSAGE

Overdose with ascorbic acid may cause nausea, vomiting, diarrhea, facial flushing, rash, headache, fatigue or disturbed sleep. If overdose of ASCOR occurs, immediately discontinue administration and treat symptoms and signs of overdose, avoiding additional intake of ascorbic acid.

11. DESCRIPTION

ASCOR (ascorbic acid injection) for intravenous use is a colorless to pale yellow, preservative-free, hypertonic, sterile, non-pyrogenic solution of ascorbic acid. ASCOR must be diluted with an appropriate infusion solution (e.g., 5% Dextrose Injection, USP, Sterile Water for Injection, USP) [see Dosage and Administration (2.1)] .

The chemical name of Ascorbic Acid is L-ascorbic acid. The molecular formula is C6H8O6. It has the following structural formula:

Each ASCOR, 50 mL, Pharmacy Bulk Package vial contains 25,000 mg ascorbic acid, equivalent to 28,125 mg sodium ascorbate.

Each mL of ASCOR contains 500 mg of ascorbic acid
(equivalent to 562.5 mg of sodium ascorbate which amounts
to 65 mg sodium/mL of ASCOR), 130 mg of Sodium
bicarbonate, and 0.25mg of edetate disodium. Sodium
hydroxide is added for pH adjustment (pH range 5.6-6.6).
It contains no bacteriostatic or antimicrobial agent.

12. CLINICAL PHARMACOLOGY

12.1 Mechanism of Action

The exact mechanism of action of ascorbic acid for the treatment of symptoms and signs of scurvy (a disorder caused by severe deficiency in vitamin C) is unknown; however, administration of ascorbic acid in patients with scurvy is thought to restore the body pool of ascorbic acid.

12.3 Pharmacokinetics

In a single pharmacokinetic study, healthy male and female adults (n=8) were given a single intravenous dose of 1000 mg ascorbic acid (5 times the largest recommended single dose) infused over a 30 minute period. The mean peak exposure to ascorbic acid was 436.2 µM and occurred at the end of the 30 minute infusion.

Distribution

Ascorbic acid is distributed widely in the body, with large concentrations found in the liver, leukocytes, platelets, glandular tissues, and lens of the eye. Based on data from oral exposure, ascorbic acid is known to be distributed into breast milk and crosses the placental barrier.

Elimination

When the body is saturated with ascorbic acid, the plasma concentration will be about the same as that of the renal threshold; if further amounts are then administered, most of it is excreted in the urine. When body tissues are not saturated and plasma concentration is low, administration of ascorbic acid results in little or no renal excretion. The mean±SD (N=3) half-life observed in the single dose PK study as described above, was 7.4±1.4 h.

Metabolism

A major route of metabolism of ascorbic acid involves its conversion to urinary oxalate, presumably through intermediate formation of its oxidized product, dehydroascorbic acid.

Excretion

There is a renal threshold for ascorbic acid (v[A1] itamin C); the vitamin is excreted by the kidney in large amounts only when the plasma concentration exceeds this threshold, which is approximately 1.4 mg/100 mL.

12.1 Mechanism of Action

The exact mechanism of action of ascorbic acid for the treatment of symptoms and signs of scurvy (a disorder caused by severe deficiency in vitamin C) is unknown; however, administration of ascorbic acid in patients with scurvy is thought to restore the body pool of ascorbic acid.

12.3 Pharmacokinetics

In a single pharmacokinetic study, healthy male and female adults (n=8) were given a single intravenous dose of 1000 mg ascorbic acid (5 times the largest recommended single dose) infused over a 30 minute period. The mean peak exposure to ascorbic acid was 436.2 µM and occurred at the end of the 30 minute infusion.

Distribution

Ascorbic acid is distributed widely in the body, with large concentrations found in the liver, leukocytes, platelets, glandular tissues, and lens of the eye. Based on data from oral exposure, ascorbic acid is known to be distributed into breast milk and crosses the placental barrier.

Elimination

When the body is saturated with ascorbic acid, the plasma concentration will be about the same as that of the renal threshold; if further amounts are then administered, most of it is excreted in the urine. When body tissues are not saturated and plasma concentration is low, administration of ascorbic acid results in little or no renal excretion. The mean±SD (N=3) half-life observed in the single dose PK study as described above, was 7.4±1.4 h.

Metabolism

A major route of metabolism of ascorbic acid involves its conversion to urinary oxalate, presumably through intermediate formation of its oxidized product, dehydroascorbic acid.

Excretion

There is a renal threshold for ascorbic acid (Vitamin C); the vitamin is excreted by the kidney in large amounts only when the plasma concentration exceeds this threshold, which is approximately 1.4 mg/100 mL.

13. NONCLINICAL TOXICOLOGY

13.1 Carcinogenesis, Mutagenesis, Impairment of Fertility

Carcinogenicity, mutagenicity, and fertility studies have not been performed with ASCOR.

13.1 Carcinogenesis, Mutagenesis, Impairment of Fertility

Carcinogenicity, mutagenicity, and fertility studies have not been performed with ASCOR.

16. HOW SUPPLIED/STORAGE AND HANDLING

ASCOR for intravenous use is a colorless to pale yellow solution supplied as:

- NDC 67157-101-50 One 25,000 mg/50 mL (500 mg/mL) Pharmacy Bulk Package vial
- NDC 67157-101-51 Tray pack of twenty five 25,000 mg/50 mL (500 mg/mL) Pharmacy Bulk Package vials

Store in a refrigerator at 2° to 8°C (36° to 46°F).

Protect from light. This product contains no preservative. See Dosage and Administration (2.1), for detailed instructions on preparation, dilution, and administration of ASCOR. Excursions to ambient conditions for up to 30 days during storage or shipping are acceptable.

17. PATIENT COUNSELING INFORMATION

- Inform patients that treatment with ASCOR may increase their risk of oxalate nephropathy [see Warnings and Precautions (5.1)] .
- Inform patients that treatment with ASCOR may impact laboratory results, including blood and urine glucose tests, up to 24 hours after infusion [see Warnings and Precautions (5.3)].
- Inform patients with glucose-6-phosphate dehydrogenase deficiency that treatment with ASCOR may increase their risk of hemolysis [see Warnings and Precautions (5.2)].

Manufactured By:

McGuff Pharmaceuticals, Inc., Santa Ana, CA 92704